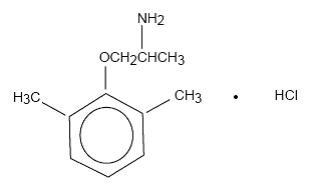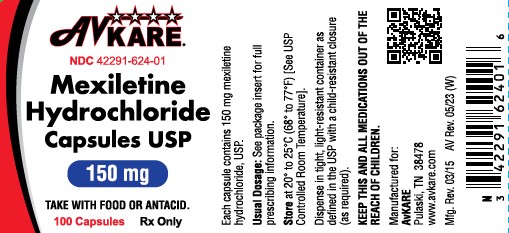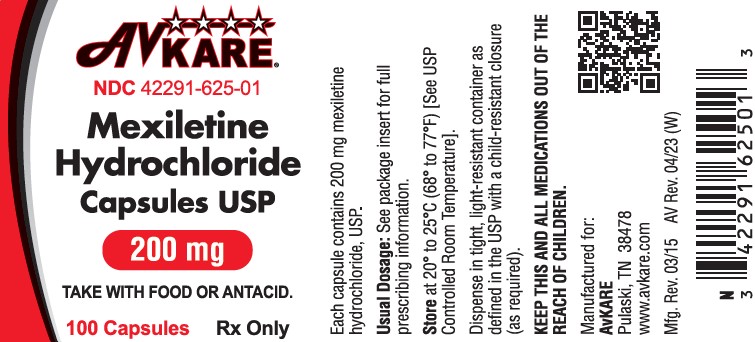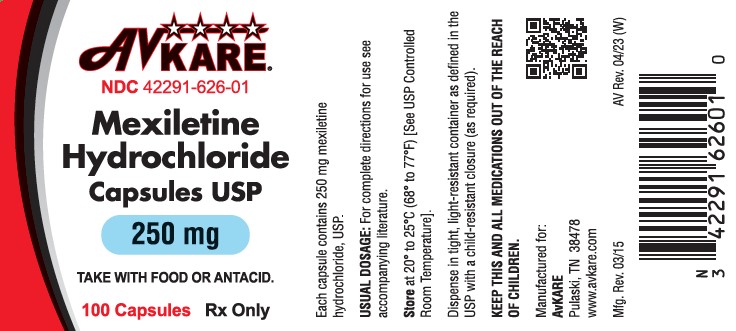 DRUG LABEL: Mexiletine Hydrochloride
NDC: 42291-624 | Form: CAPSULE
Manufacturer: AvKARE
Category: prescription | Type: HUMAN PRESCRIPTION DRUG LABEL
Date: 20260115

ACTIVE INGREDIENTS: MEXILETINE HYDROCHLORIDE 150 mg/1 1
INACTIVE INGREDIENTS: SILICON DIOXIDE; MAGNESIUM STEARATE; STARCH, CORN; FD&C YELLOW NO. 6; GELATIN; TITANIUM DIOXIDE; D&C RED NO. 28; FD&C BLUE NO. 1; AMMONIA; FERROSOFERRIC OXIDE; D&C YELLOW NO. 10; ALCOHOL; FD&C BLUE NO. 2; FD&C RED NO. 40; ISOPROPYL ALCOHOL; BUTYL ALCOHOL; PROPYLENE GLYCOL; SHELLAC

Mexiletine Hydrochloride Capsules USP
Rx Only

DESCRIPTION

Mexiletine hydrochloride, USP is an orally active antiarrhythmic agent. It is a white to off-white crystalline powder with slightly bitter taste, freely soluble in water and in alcohol. Mexiletine hydrochloride, USP has a pKa of 9.2. The chemical name of mexiletine hydrochloride, USP is 1-methyl-2-(2,6-xylyloxy)ethylamine hydrochloride and its structural formula is:

C11H17NO •HCl M.W. 215.72

Each capsule for oral administration, contains 150 mg, 200 mg, or 250 mg of mexiletine hydrochloride, USP. 100 mg of mexiletine hydrochloride, USP is equivalent to 83.31 mg of mexiletine base. In addition, each capsule contains the following excipients: colloidal silicon dioxide, magnesium stearate and pregelatinized corn starch. The capsule shell contains: FD&C Yellow #6, gelatin and titanium dioxide. The 150 mg capsule also contains: D&C Red #28 and FD&C Blue #1 and the 250 mg capsule also contains: D&C Yellow #10 and FD&C Blue #1. The imprinting ink contains: ammonium hydroxide, black iron oxide, D&C Yellow #10, ethyl alcohol, FD&C Blue #1, FD&C Blue #2, FD&C Red #40, isopropyl alcohol, n-butyl alcohol, propylene glycol and shellac.

CLINICAL PHARMACOLOGY

Mechanism of Action

Mexiletine hydrochloride is a local anesthetic, antiarrhythmic agent, structurally similar to lidocaine, but orally active. In animal studies, mexiletine has been shown to be effective in the suppression of induced ventricular arrhythmias, including those induced by glycoside toxicity and coronary artery ligation. Mexiletine, like lidocaine, inhibits the inward sodium current, thus reducing the rate of rise of the action potential, Phase 0. Mexiletine decreased the effective refractory period (ERP) in Purkinje fibers. The decrease in ERP was of lesser magnitude than the decrease in action potential duration (APD), with a resulting increase in the ERP/APD ratio.

Electrophysiology in Man

Mexiletine is a Class 1B antiarrhythmic compound with electrophysiologic properties in man similar to those of lidocaine, but dissimilar from quinidine, procainamide, and disopyramide.

In patients with normal conduction systems, mexiletine has a minimal effect on cardiac impulse generation and propagation. In clinical trials, no development of second-degree or third degree AV block was observed. Mexiletine did not prolong ventricular depolarization (QRS duration) or repolarization (QT intervals) as measured by electrocardiography. Theoretically, therefore, mexiletine may be useful in the treatment of ventricular arrhythmias associated with a prolonged QT interval.

In patients with preexisting conduction defects, depression of the sinus rate, prolongation of sinus node recovery time, decreased conduction velocity and increased effective refractory period of the intraventricular conduction system have occasionally been observed.

The antiarrhythmic effect of mexiletine has been established in controlled comparative trials against placebo, quinidine, procainamide and disopyramide. Mexiletine hydrochloride, at doses of 200 to 400 mg q8h, produced a significant reduction of ventricular premature beats, paired beats, and episodes of non-sustained ventricular tachycardia compared to placebo and was similar in effectiveness to the active agents. Among all patients entered into the studies, about 30% in each treatment group had a 70% or greater reduction in PVC count and about 40% failed to complete the 3 month studies because of adverse effects. Follow-up of patients from the controlled trials has demonstrated continued effectiveness of mexiletine in long-term use.

Hemodynamics

Hemodynamic studies in a limited number of patients, with normal or abnormal myocardial function, following oral administration of mexiletine hydrochloride, have shown small, usually not statistically significant, decreases in cardiac output and increases in systemic vascular resistance, but no significant negative inotropic effect. Blood pressure and pulse rate remain essentially unchanged. Mild depression of myocardial function, similar to that produced by lidocaine, has occasionally been observed following intravenous mexiletine therapy in patients with cardiac disease.

Pharmacokinetics

Mexiletine is well absorbed (~90%) from the gastrointestinal tract. Unlike lidocaine, its first-pass metabolism is low. Peak blood levels are reached in two to three hours. In normal subjects, the plasma elimination half-life of mexiletine is approximately 10 to 12 hours. It is 50 to 60% bound to plasma protein, with a volume of distribution of 5 to 7 liters/kg. Mexiletine is mainly metabolized in the liver, the primary pathway being CYP2D6 metabolism, although it is also a substrate for CYP1A2. With involvement of CYP2D6, there can be either poor or extensive metabolizer phenotypes. Since approximately 90% of mexiletine hydrochloride is metabolized in the liver into inactive metabolites, pathological changes in the liver can restrict hepatic clearance of mexiletine hydrochloride and its metabolites. The metabolic degradation proceeds via various pathways including aromatic and aliphatic hydroxylation, dealkylation, deamination and N-oxidation. Several of the resulting metabolites are submitted to further conjugation with glucuronic acid (phase II metabolism); among these are the major metabolites p-hydroxymexiletine, hydroxy-methylmexiletine and N-hydroxy-mexiletine. Approximately 10% is excreted unchanged by the kidney. While urinary pH does not normally have much influence on elimination, marked changes in urinary pH influence the rate of excretion: acidification accelerates excretion, while alkalinization retards it.

Several metabolites of mexiletine have shown minimal antiarrhythmics activity in animal models. The most active is the minor metabolite N-methylmexiletine, which is less than 20% as potent as mexiletine. The urinary excretion of N-methylmexiletine in man is less than 0.5%. Thus the therapeutic activity of mexiletine is due to the parent compound.

Hepatic impairment prolongs the elimination half-life of mexiletine. In eight patients with moderate to severe liver disease, the mean half-life was approximately 25 hours.

Consistent with the limited renal elimination of mexiletine, little change in the half-life has been detected in patients with reduced renal function. In eight patients with creatinine clearance less than 10 mL/min, the mean plasma elimination half-life was 15.7 hours; in seven patients with creatinine clearance between 11 to 40 mL/min, the mean half-life was 13.4 hours.

The absorption rate of mexiletine is reduced in clinical situations such as acute myocardial infarction in which gastric emptying time is increased. Narcotics, atropine and magnesium-aluminum hydroxide have also been reported to slow the absorption of mexiletine. Metoclopramide has been reported to accelerate absorption.

Mexiletine plasma levels of at least 0.5 mcg/mL are generally required for therapeutic response. An increase in the frequency of central nervous system adverse effects has been observed when plasma levels exceed 2 mcg/mL. Thus the therapeutic range is approximately 0.5 to 2 mcg/mL. Plasma levels within the therapeutic range can be attained with either three times daily or twice daily dosing but peak to trough differences are greater with the latter regimen, creating the possibility of adverse effects at peak and arrhythmic escape at trough. Nevertheless, some patients may be transferred successfully to the twice daily regimen. (See DOSAGE AND ADMINISTRATION.)

INDICATIONS AND USAGE

Mexiletine hydrochloride capsules USP are indicated for the treatment of documented ventricular arrhythmias, such as sustained ventricular tachycardia, that, in the judgment of the physician, are life-threatening. Because of the proarrhythmic effects of mexiletine, its use with lesser arrhythmias is generally not recommended. Treatment of patients with asymptomatic ventricular premature contractions should be avoided.

Initiation of mexiletine treatment, as with other antiarrhythmic agents used to treat life-threatening arrhythmias, should be carried out in the hospital.

Antiarrhythmic drugs have not been shown to enhance survival in patients with ventricular arrhythmias.

CONTRAINDICATIONS

Mexiletine hydrochloride capsules are contraindicated in the presence of cardiogenic shock or pre-existing second-or third-degree AV block (if no pacemaker is present).

BOXED WARNING

WARNINGS

Mortality

In the National Heart, Lung and Blood Institute’s Cardiac Arrhythmia Suppression Trial (CAST), a long-term, multicentered, randomized, double-blind study in patients with asymptomatic non-life-threatening ventricular arrhythmias who had a myocardial infarction more than six days but less than two years previously, an excessive mortality or non-fatal cardiac arrest rate (7.7%) was seen in patients treated with encainide or flecainide compared with that seen in patients assigned to carefully matched placebo-treated groups (3.0%). The average duration of treatment with encainide or flecainide in this study was ten months.

The applicability of the CAST results to other populations (e.g., those without recent myocardial infarction) is uncertain. Considering the known proarrhythmic properties of mexiletine and the lack of evidence of improved survival for any antiarrhythmic drug in patients without life-threatening arrhythmias, the use of mexiletine as well as other antiarrhythmic agents should be reserved for patients with life-threatening ventricular arrhythmia.

Acute Liver Injury

In postmarketing experience abnormal liver function tests have been reported, some in the first few weeks of therapy with mexiletine hydrochloride. Most of these have been observed in the setting of congestive heart failure or ischemia and their relationship to mexiletine hydrochloride has not been established.

Drug Reactions with Eosinophilia and Systemic Symptoms (DRESS)

Drug reactions with eosinophilia and systemic symptoms (DRESS) have been reported in patients taking mexiletine. DRESS typically presents with eosinophilia, fever, rash, and/or lymphadenopathy in association with other organ involvement, such as hepatitis, nephritis, hematologic abnormalities, myocarditis, or myositis, sometimes resembling an acute viral infection. Discontinue mexiletine if DRESS is suspected.

PRECAUTIONS

General

If a ventricular pacemaker is operative, patients with second or third degree heart block may be treated with mexiletine hydrochloride if continuously monitored. A limited number of patients (45 of 475 in controlled clinical trials) with preexisting first degree AV block were treated with mexiletine; none of these patients developed second or third degree AV block. Caution should be exercised when it is used in such patients or in patients with preexisting sinus node dysfunction or intraventricular conduction abnormalities.

Like other antiarrhythmics mexiletine hydrochloride can cause worsening of arrhythmias. This has been uncommon in patients with less serious arrhythmias (frequent premature beats or nonsustained ventricular tachycardia: see ADVERSE REACTIONS), but is of greater concern in patients with life-threatening arrhythmias such as sustained ventricular tachycardia. In patients with such arrhythmias subjected to programmed electrical stimulation or to exercise provocation, 10 to 15% of patients had exacerbation of the arrhythmia, a rate not greater than that of other agents.

Mexiletine should be used with caution in patients with hypotension and severe congestive heart failure because of the potential for aggravating these conditions.

Since mexiletine is metabolized in the liver, and hepatic impairment has been reported to prolong the elimination half-life of mexiletine, patients with liver disease should be followed carefully while receiving mexiletine. The same caution should be observed in patients with hepatic dysfunction secondary to congestive heart failure.

Concurrent drug therapy or dietary regimens which may markedly alter urinary pH should be avoided during mexiletine hydrochloride therapy. The minor fluctuations in urinary pH associated with normal diet do not affect the excretion of mexiletine.

SGOT Elevation and Liver Injury

In three month controlled trials, elevations of SGOT greater than three times the upper limit of normal occurred in about 1% of both mexiletine-treated and control patients. Approximately 2% of patients in the mexiletine compassionate use program had elevations of SGOT greater than or equal to three times the upper limit of normal. These elevations frequently occurred in association with identifiable clinical events and therapeutic measures such as congestive heart failure, acute myocardial infarction, blood transfusions and other medications. These elevations were often asymptomatic and transient, usually not associated with elevated bilirubin levels and usually did not require discontinuation of therapy. Marked elevations of SGOT (> 1000 U/L) were seen before death in four patients with end-stage cardiac disease (severe congestive heart failure, cardiogenic shock).

Rare instances of severe liver injury, including hepatic necrosis, have been reported in association with mexiletine treatment. It is recommended that patients in whom an abnormal liver test has occurred, or who have signs of symptoms suggesting liver dysfunction, be carefully evaluated. If persistent or worsening elevation of hepatic enzymes is detected, consideration should be given to discontinuing therapy.

Blood Dyscrasias

Among 10,867 patients treated with mexiletine in the compassionate use program, marked leukopenia (neutrophils less than 1000/mm^3) or agranulocytosis were seen in 0.06% and milder depressions of leukocytes were seen in 0.08%, and thrombocytopenia was observed in 0.16%. Many of these patients were seriously ill and receiving concomitant medications with known hematologic adverse effects. Rechallenge with mexiletine in several cases was negative. Marked leukopenia or agranulocytosis did not occur in any patient receiving mexiletine alone; five of the six cases of agranulocytosis were associated with procainamide (sustained release preparations in four) and one with vinblastine. If significant hematologic changes are observed, the patient should be carefully evaluated, and, if warranted, mexiletine should be discontinued. Blood counts usually return to normal within a month of discontinuation (see ADVERSE REACTIONS).

Convulsions (seizures) did not occur in mexiletine controlled clinical trials. In the compassionate use program, convulsions were reported in about 2 of 1000 patients. Twenty-eight percent of these patients discontinued therapy. Convulsions were reported in patients with and without a prior history of seizures. Mexiletine should be used with caution in patients with known seizure disorder.

Drug Interactions

Since mexiletine hydrochloride is a substrate for the metabolic pathways involving CYP2D6 and CYP1A2 enzymes, inhibition or induction of either of these enzymes would be expected to alter mexiletine plasma concentrations. In a formal, single-dose interaction study (n = 6 males) the clearance of mexiletine was decreased by 38% following the coadministration of fluvoxamine, an inhibitor of CYP1A2. In another formal study (n = 8 extensive and n = 7 poor metabolizers of CYP2D6), coadministration of propafenone did not alter the kinetics of mexiletine in the poor CYP2D6 metabolizer group. However, the metabolic clearance of mexiletine in the extensive metabolizer phenotype decreased by about 70% making the poor and extensive metabolizer groups indistinguishable. In this crossover steady state study, the pharmacokinetics of propafenone were unaffected in either phenotype by the coadministration of mexiletine. Addition of mexiletine to propafenone did not lead to further electrocardiographic parameters changes of QRS, QTC, RR, and PR intervals than propafenone alone. When concomitant administration of either of these two drugs is initiated, the dose of mexiletine should be slowly titrated to desired effect.

In a large compassionate use program mexiletine has been used concurrently with commonly employed antianginal, antihypertensive, and anticoagulant drugs without observed interactions. A variety of antiarrhythmics such as quinidine or propranolol were also added, sometimes with improved control of ventricular ectopy. When phenytoin or other hepatic enzyme inducers such as rifampin and phenobarbital have been taken concurrently with mexiletine, lowered mexiletine plasma levels have been reported. Monitoring of mexiletine plasma levels is recommended during such concurrent use to avoid ineffective therapy.

In a formal study, benzodiazepines were shown not to affect mexiletine plasma concentrations. ECG intervals (PR, QRS, and QT) were not affected by concurrent mexiletine and digoxin, diuretics, or propranolol.

Concurrent administration of cimetidine and mexiletine has been reported to increase, decrease, or leave unchanged mexiletine plasma levels; therefore patients should be followed carefully during concurrent therapy.

Mexiletine does not alter serum digoxin levels but magnesium-aluminum hydroxide, when used to treat gastrointestinal symptoms due to mexiletine, has been reported to lower serum digoxin levels.

Concurrent use of mexiletine and theophylline may lead to increased plasma theophylline levels. One controlled study in eight normal subjects showed a 72% mean increase (range

35 to 136%) in plasma theophylline levels. This increase was observed at the first test point which was the second day after starting mexiletine. Theophylline plasma levels returned to pre-mexiletine values within 48 hours after discontinuing mexiletine. If mexiletine and theophylline are to be used concurrently, theophylline blood levels should be monitored, particularly when the mexiletine dose is changed. An appropriate adjustment in theophylline dose should be considered.

Additionally, in one controlled study in five normal subjects and seven patients, the clearance of caffeine was decreased 50% following the administration of mexiletine.

Carcinogenesis, Mutagenesis, Impairment of Fertility

Studies of carcinogenesis in rats (24 months) and mice (18 months) did not demonstrate any tumorigenic potential. Mexiletine was found to be non-mutagenic in the Ames test. Mexiletine did not impair fertility in the rat.

Pregnancy

Teratogenic Effects

Pregnancy category C

Reproduction studies performed with mexiletine in rats, mice and rabbits at doses up to four times the maximum human oral dose (24 mg/kg in a 50 kg patient) revealed no evidence of teratogenicity or impaired fertility but did show an increase in fetal resorption. There are no adequate and well-controlled studies in pregnant women; this drug should be used in pregnancy only if the potential benefit justifies the potential risk to the fetus.

Nursing Mothers

Mexiletine appears in human milk in concentrations similar to those observed in plasma. Therefore, if the use of mexiletine hydrochloride is deemed essential, an alternative method of infant feeding should be considered.

Pediatric Use

Safety and effectiveness in pediatric patients have not been established.

ADVERSE REACTIONS

Mexiletine hydrochloride commonly produces reversible gastrointestinal and nervous system adverse reactions but is otherwise well tolerated. Mexiletine has been evaluated in 483 patients in one month and three month controlled studies and in over 10,000 patients in a large compassionate use program. Dosages in the controlled studies ranged from 600 to 1200 mg/day; some patients (8%) in the compassionate use program were treated with higher daily doses (1600 to 3200 mg/day). In the three month controlled trials comparing mexiletine to quinidine, procainamide and disopyramide, the most frequent adverse reactions were upper gastrointestinal distress (41%), lightheadedness (10.5%), tremor (12.6%) and coordination difficulties (10.2%). Similar frequency and incidence were observed in the one month placebo-controlled trial. Although these reactions were generally not serious, and were dose-related and reversible with a reduction in dosage, by taking the drug with food or antacid or by therapy discontinuation, they led to therapy discontinuation in 40% of patients in the controlled trials. Table 1 presents the adverse events reported in the one-month placebo-controlled trial.

Table 1: Comparative Incidence (%) of Adverse Events Among Patients Treated with Mexiletine and Placebo in the 4 Week, Double-Blind Crossover Trial

 | Mexiletine N = 53 | Placebo N = 49
Cardiovascular
Palpitations | 7.5 | 10.2
Chest Pain | 7.5 | 4.1
Increased Ventricular Arrythmia/PVCs | 1.9 | -
Digestive
Nausea/Vomiting/Heartburn | 39.6 | 6.1
Central Nervous System
Dizziness/Lightheadedness | 26.4 | 14.3
Tremor | 13.2 | -
Nervousness | 11.3 | 6.1
Coordination Difficulties | 9.4 | -
Changes in Sleep Habits | 7.5 | 16.3
Paresthesias/Numbness | 3.8 | 2
Weakness | 1.9 | 4.1
Fatigue | 1.9 | 2
Tinnitus | 1.9 | 4.1
Confusion/Clouded Sensorium | 1.9 | 2
Other
Headache | 7.5 | 6.1
Blurred Vision/Visual Disturbances | 7.5 | 2
Dyspnea/Respiratory | 5.7 | 10.2
Rash | 3.8 | 2
Non-specific Edema | 3.8 | -

Table 2 presents the adverse reactions occurring in one percent or more of patients in the three month controlled studies.

Table 2: Comparative Incidence (%) of Adverse Events Among Patients Treated with Mexiletine or Control Drugs in the 12 Week Double-Blind Trials

 | Mexiletine N = 430 | Quinidine N = 262 | Procainamide N = 78 | Disopyramide N = 69
Cardiovascular
Palpitations | 4.3 | 4.6 | 1.3 | 5.8
Chest Pain | 2.6 | 3.4 | 1.3 | 2.9
Angina/Angina-like Pain | 1.7 | 1.9 | 2.6 | 2.9
Increased Ventricular Arrhythmias/PVCs | 1 | 2.7 | 2.6 | -
Digestive
Nausea/Vomiting/ Heartburn | 39.3 | 21.4 | 33.3 | 14.5
Diarrhea | 5.2 | 33.2 | 2.6 | 8.7
Constipation | 4 | - | 6.4 | 11.6
Changes in Appetite | 2.6 | 1.9 | - | -
Abdominal Pain/Cramps/ Discomfort | 1.2 | 1.5 | - | 1.4
Central Nervous System
Dizziness/Lightheadedness | 18.9 | 14.1 | 14.1 | 2.9
Tremor | 13.2 | 2.3 | 3.8 | 1.4
Coordination Difficulties | 9.7 | 1.1 | 1.3 | -
Changes in Sleep Habits | 7.1 | 2.7 | 11.5 | 8.7
Weakness | 5 | 5.3 | 7.7 | 2.9
Nervousness | 5 | 1.9 | 6.4 | 5.8
Fatigue | 3.8 | 5.7 | 5.1 | 1.4
Speech Difficulties | 2.6 | 0.4 | - | -
Confusion/Clouded Sensorium | 2.6 | - | 3.8 | -
Paresthesias/Numbness | 2.4 | 2.3 | 2.6 | -
Tinnitus | 2.4 | 1.5 | - | -
Depression | 2.4 | 1.1 | 1.3 | 1.4
Other
Blurred Vision/Visual Disturbances | 5.7 | 3.1 | 5.1 | 7.2
Headache | 5.7 | 6.9 | 7.7 | 4.3
Rash | 4.2 | 3.8 | 10.3 | 1.4
Dyspnea/Respiratory | 3.3 | 3.1 | 5.1 | 2.9
Dry Mouth | 2.8 | 1.9 | 5.1 | 14.5
Arthralgia | 1.7 | 2.3 | 5.1 | 1.4
Fever | 1.2 | 3.1 | 2.6 | -

Less than 1%: Syncope, edema, hot flashes, hypertension, short-term memory loss, loss of consciousness, other psychological changes, diaphoresis, urinary hesitancy/retention, malaise, impotence/decreased libido, pharyngitis, congestive heart failure.

An additional group of over 10,000 patients has been treated in a program allowing administration of mexiletine hydrochloride under compassionate use circumstances. These patients were seriously ill with the large majority on multiple drug therapy. Twenty-four percent of the patients continued in the program for one year or longer. Adverse reactions leading to therapy discontinuation occurred in 15 percent of patients (usually upper gastrointestinal system or nervous system effects). In general, the more common adverse reactions were similar to those in the controlled trials. Less common adverse events possibly related to mexiletine use include:

Cardiovascular System

Syncope and hypotension, each about 6 in 1000; bradycardia, about 4 in 1000; angina/angina-like pain, about 3 in 1000; edema, atrioventricular block/conduction disturbances and hot flashes, each about 2 in 1000; atrial arrhythmias, hypertension and cardiogenic shock, each about 1 in 1000.

Central Nervous System

Short-term memory loss, about 9 in 1000 patients; hallucinations and other psychological changes, each about 3 in 1000; psychosis and convulsions/seizures, each about 2 in 1000; loss of consciousness, about 6 in 10,000.

Digestive

Dysphagia, about 2 in 1000; peptic ulcer, about 8 in 10,000; upper gastrointestinal bleeding, about 7 in 10,000; esophageal ulceration, about 1 in 10,000. Rare cases of severe hepatitis/acute hepatic necrosis.

Skin

Rare cases of exfoliative dermatitis and Stevens-Johnson syndrome with mexiletine treatment have been reported.

Laboratory

Abnormal liver function tests, about 5 in 1000; positive ANA and thrombocytopenia, each about 2 in 1000; leukopenia (including neutropenia and agranulocytosis), about 1 in 1000; myelofibrosis, about 2 in 10,000 patients.

Other

Diaphoresis, about 6 in 1000; altered taste, about 5 in 1000; salivary changes, hair loss and impotence/decreased libido, each about 4 in 1000; malaise, about 3 in 1000; urinary hesitancy/retention, each about 2 in 1000; hiccups, dry skin, laryngeal and pharyngeal changes and changes in oral mucous membranes, each about 1 in 1000; SLE syndrome, about 4 in 10,000.

Hematology

Blood dyscrasias were not seen in the controlled trials but did occur among 10,867 patients treated with mexiletine in the compassionate use program (see PRECAUTIONS).

Myelofibrosis was reported in two patients in the compassionate use program; one was receiving long-term thiotepa therapy and the other had pretreatment myeloid abnormalities.

In postmarketing experience, there have been isolated, spontaneous reports of pulmonary changes including pulmonary infiltration and pulmonary fibrosis during mexiletine therapy with or without other drugs or diseases that are known to produce pulmonary toxicity. A causal relationship to mexiletine therapy has not been established. In addition, there have been isolated reports of drowsiness, nystagmus, ataxia, dyspepsia, hypersensitivity reaction, and exacerbation of congestive heart failure in patients with preexisting compromised ventricular function. There have been rare reports of pancreatitis associated with mexiletine treatment.

OVERDOSAGE

Clinical findings associated with mexiletine overdosage have included drowsiness, confusion, nausea, hypotension, sinus bradycardia, paresthesia, seizures, bundle branch block, AV heart block, asystole, ventricular tachyarrythmia, including ventricular fibrillation, cardiovascular collapse and coma. The lowest known dose in a fatality case was 4.4 g with postmortem serum mexiletine level of 34 to 37 mcg/mL (Jequier P. et. al., Lancet 1976: 1 (7956): 429). Patients have recovered from ingestion of 4 g to 18 g of mexiletine (Frank S. E. et. al., Am J Emerg Med 1991: 9:43-48).

There is no specific antidote for mexiletine. Management of mexiletine overdosage includes general supportive measures, close observation and monitoring of vital signs. In addition, the use of pharmacologic interventions (e.g., pressor agents, atropine or anticonvulsants) or transvenous cardiac pacing is suggested, depending on the patient’s clinical condition.

DOSAGE AND ADMINISTRATION

The dosage of mexiletine hydrochloride must be individualized on the basis of response and tolerance, both of which are dose-related. Administration with food or antacid is recommended. Initiate mexiletine therapy with 200 mg every eight hours when rapid control of arrhythmia is not essential. A minimum of two to three days between dose adjustments is recommended. Dose may be adjusted in 50 or 100 mg increments up or down.

As with any antiarrhythmic drug, clinical and electrocardiographic evaluation (including Holter monitoring if necessary for evaluation) are needed to determine whether the desired antiarrhythmic effect has been obtained and to guide titration and dose adjustment.

Satisfactory control can be achieved in most patients by 200 to 300 mg given every eight hours with food or antacid. If satisfactory response has not been achieved at 300 mg q8h, and the patient tolerates mexiletine well, a dose of 400 mg q8h may be tried. As the severity of CNS side effects increases with total daily dose, the dose should not exceed 1200 mg/day.

In general, patients with renal failure will require the usual doses of mexiletine hydrochloride. Patients with severe liver disease, however, may require lower doses and must be monitored closely. Similarly, marked right-sided congestive heart failure can reduce hepatic metabolism and reduce the needed dose. Plasma level may also be affected by certain concomitant drugs (see PRECAUTIONS, Drug Interactions).

Loading Dose

When rapid control of ventricular arrhythmia is essential, an initial loading dose of 400 mg of mexiletine hydrochloride may be administered, followed by a 200 mg dose in eight hours. Onset of therapeutic effect is usually observed within 30 minutes to two hours.

Q12H Dosage Schedule

Some patients responding to mexiletine may be transferred to a 12 hour dosage schedule to improve convenience and compliance. If adequate suppression is achieved on a mexiletine hydrochloride dose of 300 mg or less every eight hours, the same total daily dose may be given in divided doses every 12 hours while carefully monitoring the degree of suppression of ventricular ectopy. This dose may be adjusted up to a maximum of 450 mg every 12 hours to achieve the desired response.

Transferring to Mexiletine Hydrochloride

The following dosage schedule, based on theoretical considerations rather than experimental data, is suggested for transferring patients from other Class I oral antiarrhythmic agents to mexiletine: mexiletine hydrochloride treatment may be initiated with a 200 mg dose, and titrated to response as described above, 6 to 12 hours after the last dose of quinidine sulfate, 3 to 6 hours after the last dose of procainamide, 6 to 12 hours after the last dose of disopryramide or 8 to 12 hours after the last dose of tocainide.

In patients in whom withdrawal of the previous antiarrhythmic agent is likely to produce life-threatening arrhythmias, hospitalization of the patient is recommended.

When transferring from lidocaine to mexiletine, the lidocaine infusion should be stopped when the first oral dose of mexiletine hydrochloride is administered. The infusion line should be left open until suppression of the arrhythmia appears to be satisfactorily maintained. Consideration should be given to the similarity of the adverse effects of lidocaine and mexiletine and the possibility that they may be additive.

HOW SUPPLIED

Mexiletine hydrochloride capsules USP, 150 mg are white granular powder in a hard gelatin capsule with an opaque tan cap and an opaque orange body, imprinted with "N" on one side and "739" and "150" on the other in black ink. They are supplied as follows: NDC 42291-624-01 bottles of 100.

Mexiletine hydrochloride capsules USP, 200 mg are white granular powder in a hard gelatin capsule with an opaque orange cap and an opaque orange body, imprinted with "N" one one side and "740" and "200" on the other in black ink. They are supplied as follows: NDC 42291-625-01 bottles of 100.

Mexiletine hydrochloride capsules USP, 250 mg are white granular powder in a hard gelatin capsule with an opaque green cap and an opaque orange body, imprinted with "N" on one side and "741" and "250" on the other in black ink. They are supplied as follows: NDC 42291-626-01 bottles of 100.

Store at 20° to 25°C (68° to 77°F) [See USP Controlled Room Temperature].

Dispense in a tight, light-resistant container as defined in the USP, with a child-resistant closure (as required).

Manufactured For:

AvKARE

Pulaski, TN 38478

Mfg. Rev. 03/15
AV Rev. 08/18 (P)